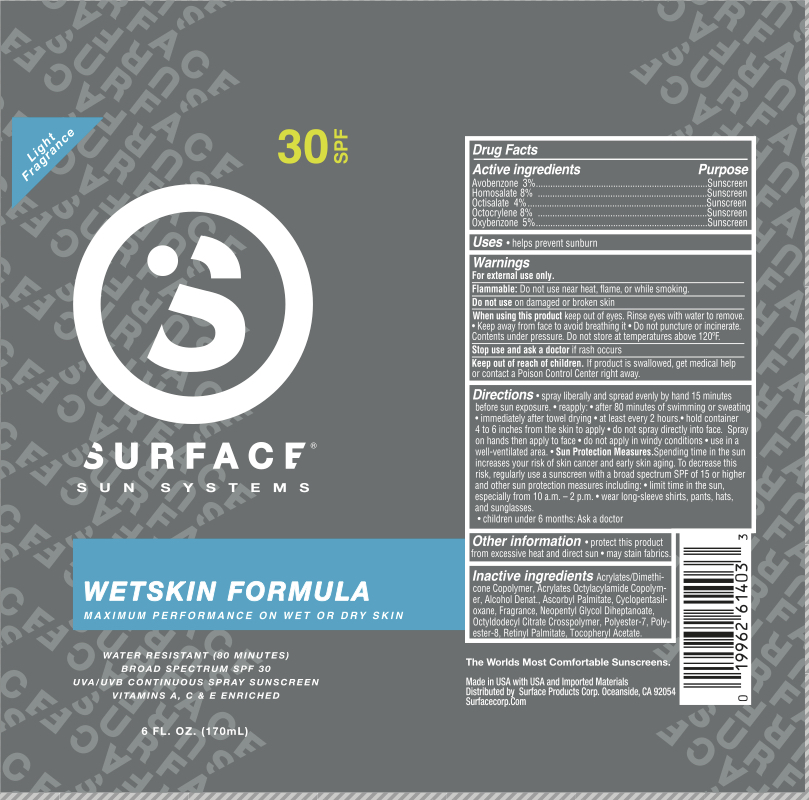 DRUG LABEL: Surface Sun Wetskin Formula SPF 30 Sunscreen
NDC: 72344-006 | Form: SPRAY
Manufacturer: Surface Products Corp
Category: otc | Type: HUMAN OTC DRUG LABEL
Date: 20180522

ACTIVE INGREDIENTS: AVOBENZONE 3 g/100 mL; HOMOSALATE 8 g/100 mL; OCTISALATE 4 g/100 mL; OXYBENZONE 5 g/100 mL; OCTOCRYLENE 8 g/100 mL
INACTIVE INGREDIENTS: DIMETHICONE; ALCOHOL; ACRYLATE/ISOBUTYL METHACRYLATE/N-TERT-OCTYLACRYLAMIDE COPOLYMER (75000 MW); NEOPENTYL GLYCOL DIHEPTANOATE; CYCLOMETHICONE 5; ASCORBYL PALMITATE; VITAMIN A PALMITATE; POLYESTER-7; POLYESTER-8 (1400 MW, CYANODIPHENYLPROPENOYL CAPPED); ALPHA-TOCOPHEROL ACETATE

Active Ingredients

Avobenzone 3%, Homosalate 8%, Octisalate 4%, Octocrylene 8%, Oxybenzone 5%

Purpose

Sunscreen

Use

Helps prevent sunburn.

Warnings

For external use only.

Flammable: do not use near heat, flame, or while smoking. Do not use on damaged or broken skin. When using this product keep out of eyes. Rinse eyes with water to remove. Keep away from face to avoid breathing it. Do not puncture or incinerate. Contents under pressure. Do not store at temperatures above 120F. Stop use and ask a doctor if rash occurs.

Keep Out of Reach of Children.

If product is swallowed, get medical help or contact a Poison Control Center right away.

Directions

Spray liberally and evenly by hand 15 minutes before sun exposure.

Reapply after:

80 minutes of sweating or swimming
immediately after towel drying
at least every 2 hours

Hold can 4-6 inches from the skin to apply. Do not spray directly into your face. Spray on hands an then apply to face. Do not apply in windy conditions. Use in a well-ventilated area.

Sun Protection Measures: Spending time in the sun increases your risk of skin cancer and early skin aging. To decrease this risk, regularly use a sunscreen with a broad spectrum SPF of 15 or higher and other sun protection measures including:
Limit time in the sun, especially from 10 a.m. - 2 p.m.
Wear long-sleeved shirts, pants, hats, and sunglasses.

Children under 6 months: ask a doctor.

Inactive Ingredients

Acrylates/Dimethicone Copolymer, Acrylates Octylacrylamide Copolymer, Alcohol Denat., Ascorbyl Palmitate, Cyclopentasiloxane, Fragrance, Neopentyl Glycol Diheptanoate, Octyldodecyl Citrate Crosspolymer, Polyester-7, Polyester-8, Retinyl Palmitate, Tocopheryl Acetate.